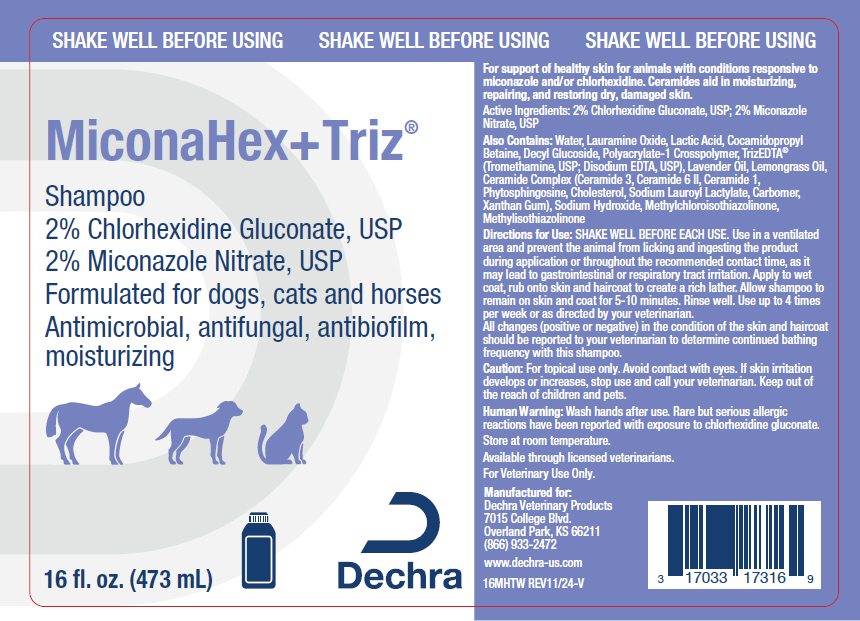 DRUG LABEL: MiconaHex plus Triz
NDC: 17033-175 | Form: SHAMPOO
Manufacturer: Dechra Veterinary Products
Category: animal | Type: OTC ANIMAL DRUG LABEL
Date: 20250606

ACTIVE INGREDIENTS: Chlorhexidine Gluconate 20 mg/1 mL; MICONAZOLE NITRATE 20 mg/1 mL

MiconaHex+Triz® Shampoo

VETERINARY INDICATIONS

For support of healthy skin for animals with conditions responsive to miconazole and/or chlorhexidine. Ceramides aid in moisturizing, repairing, and restoring dry, damaged skin.

DESCRIPTION

Active Ingredients: 2% Chlorhexidine Gluconate, USP; 2% Miconazole Nitrate, USP

Also Contains: Water, Lauramine Oxide, Lactic Acid, Cocamidopropyl Betaine, Decyl Glucoside, Polyacrylate-1 Crosspolymer, TrizEDTA® (Tromethamine, USP; Disodium EDTA, USP), Lavender Oil, Lemongrass Oil, Ceramide Complex (Ceramide 3, Ceramide 6 II, Ceramide 1, Phytosphingosine, Cholesterol, Sodium Lauroyl Lactylate, Carbomer, Xanthan Gum), Sodium Hydroxide, Methylchloroisothiazolinone, Methylisothiazolinone

DOSAGE AND ADMINISTRATION

Directions for Use: SHAKE WELL BEFORE EACH USE. Apply to wet coat, rub onto skin and haircoat to create a rich lather. Allow shampoo to remain on skin and coat for 5-10 minutes. Rinse well. Use up to 4 times per week or as directed by your veterinarian. All changes (positive or negative) in the condition of the skin and haircoat should be reported to your veterinarian to determine continued bathing frequency with this shampoo.

WARNINGS

Caution: For topical use only. Avoid contact with eyes. If skin irritation develops or increases, stop use and call your veterinarian. Keep out of the reach of children and pets.

SAFE HANDLING WARNING

Human Warning: Wash hands after use. Rare but serious allergic reactions have been reported with exposure to chlorhexidine gluconate.

STORAGE AND HANDLING

Store at room temperature.

Available through licensed veterinarians.

For Veterinary Use Only.

Manufactured for:
Dechra Veterinary Products
7015 College Blvd.
Overland Park, KS 66211
(866) 933-2472

www.dechra-us.com

16MHTW REV09/23-V

PRINCIPAL DISPLAY PANEL - 473 mL Bottle Label

SHAKE WELL BEFORE USING

MiconaHex+Triz®

Shampoo
2% Chlorhexidine Gluconate, USP
2% Miconazole Nitrate, USP
Formulated for dogs, cats and horses
Antimicrobial, antifungal, antibiofilm,
moisturizing

16 fl. oz. (473 mL)

Dechra